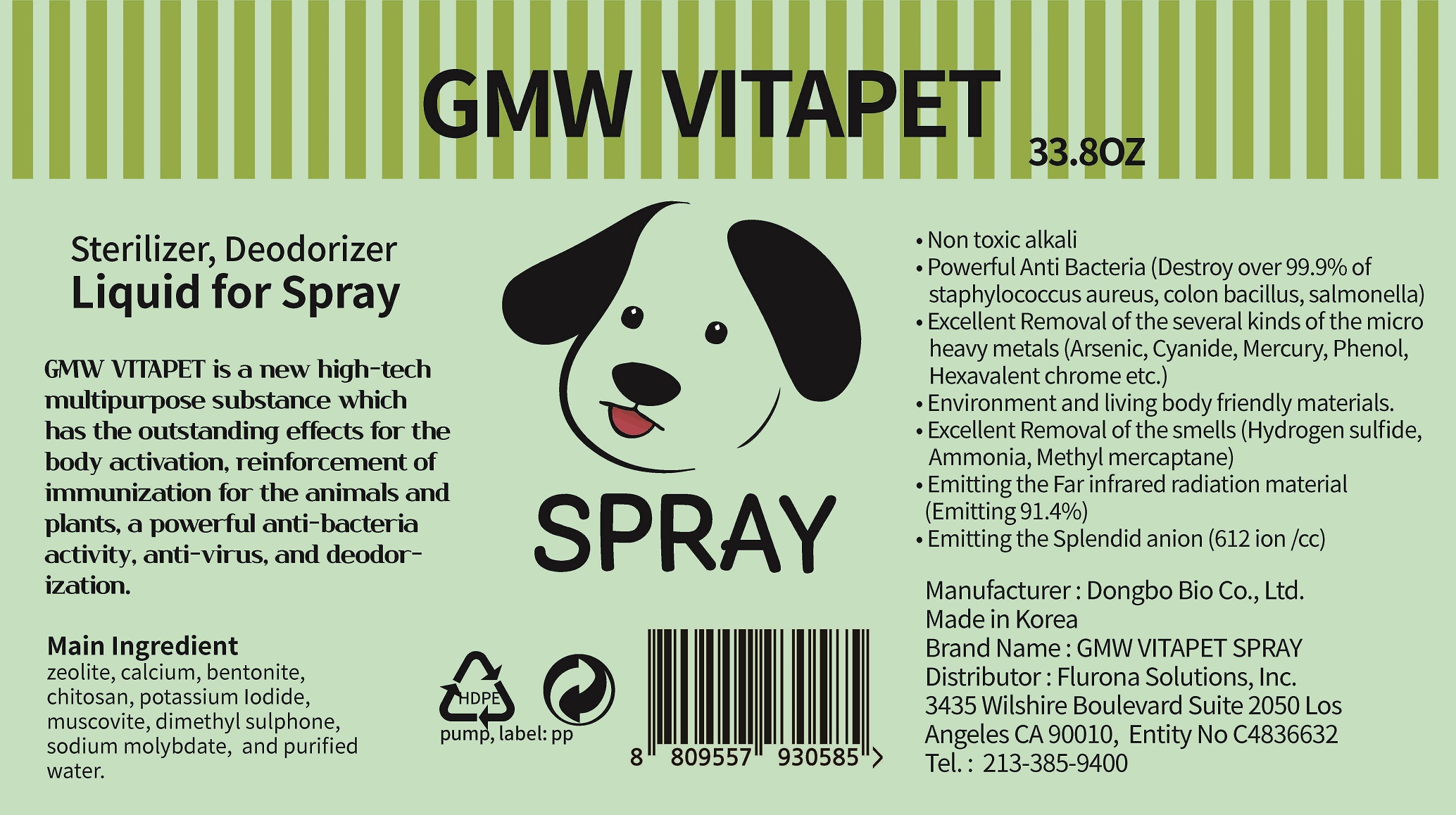 DRUG LABEL: GMW VITAPET
NDC: 74651-0008 | Form: LIQUID
Manufacturer: DONGBO BIO CO.,LTD
Category: animal | Type: OTC ANIMAL DRUG LABEL
Date: 20220504

ACTIVE INGREDIENTS: ZEOLITE A 9.2 g/100 mL
INACTIVE INGREDIENTS: WATER; CALCIUM; CHITOSAN OLIGOSACCHARIDE; IODINE

ACTIVE INGREDIENT

zeolite

INACTIVE INGREDIENT

alcium, bentonite, chitosan, potassium Iodide, muscovite, dimethyl sulphone, sodium molybdate, purified water

PURPOSE

Air Freshener
Eliminate Virus

Effective in Bird flu and Newcastle disease

Effective in foot & mouth disease, brucellosis, hog cholera and classical swine fever.

Be extinct Zika virus

Red tide and green tide treatment

Water purification

Natural ingredients for cosmetics

Sick house syndrome treatment

Additives for functional plastic, fiber and freshness box

WARNINGS

■ if following abnormal symptoms persist, discontinue use

Irritation around the eyes, ears, mucous membranes, including the mouth, under the skin irritation and rashes

■ Stop immediately and consult a doctor if you experience

1) Hypersensitivity symptoms such as erythema, itching and dermatitis.

2) Skin Irritation

3) Following Instructions when using medication

(1) For external use only (Do not use internally)

(2) Avoid getting into the eyes (if contact occurs, wash well with clean water)

■ Be careful not to inhale or use excessively for a long time (ingesting ethanol repeatedly causes irritation to mucous membranes and headaches or other symptoms may appear. When used repeatedly in the same area, skin irritation may occur.

■ Do not use the product for a long time in the same area as swelling, inflammation or sickness may occur due to absorption through the skin.

It is not recommended to use this one areas that have been medically treated with a cast or bandage.

■ Do not use in combination with soap or antibacterial cleansing agents.

• Keep Out of Reach of Children

INDICATIONS AND USAGE

■ spray a small amount into the animal, spread evenly and rub into the skin

DOSAGE AND ADMINISTRATION

for topical use only